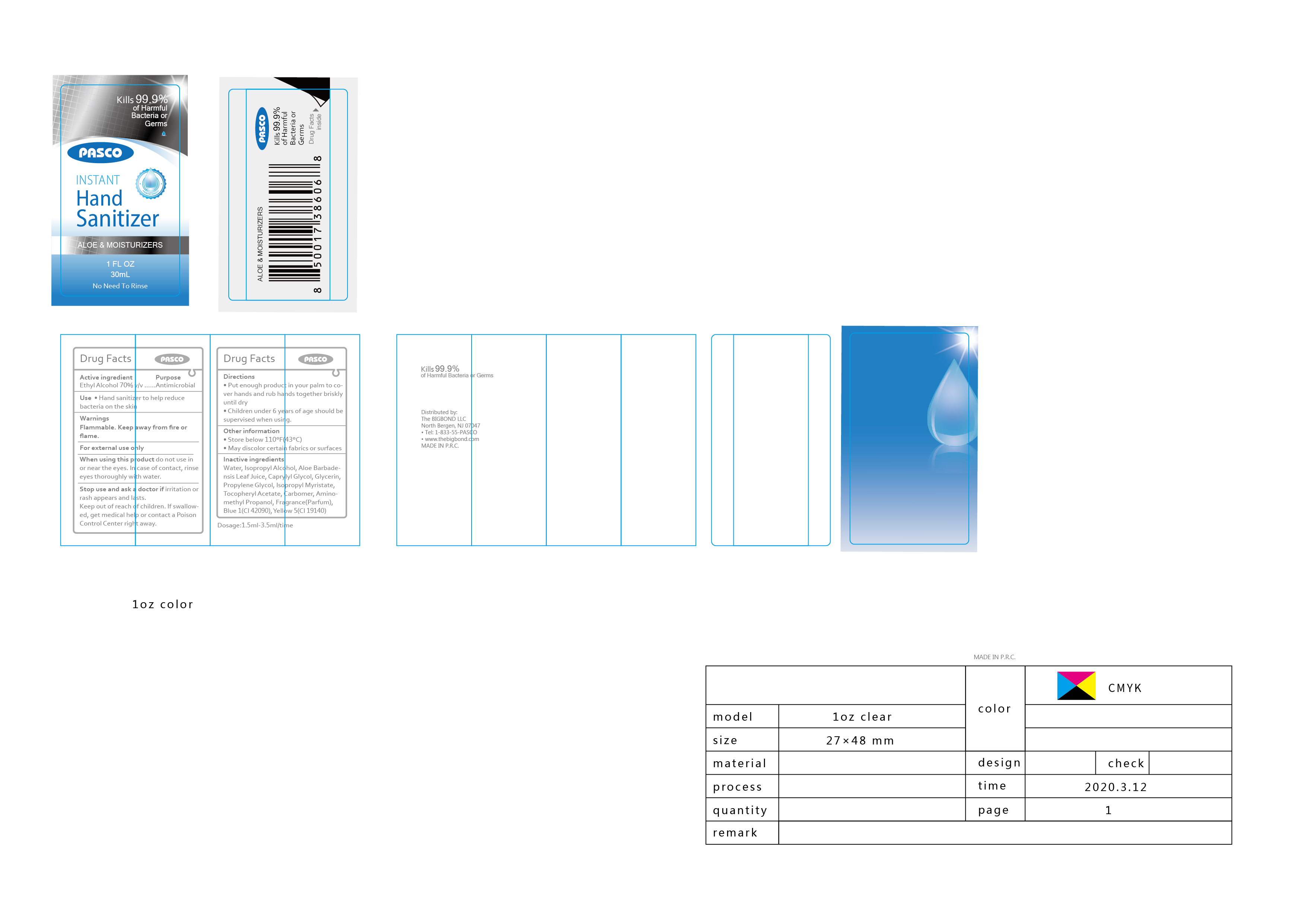 DRUG LABEL: Instant hand sanitizer
NDC: 87052-111 | Form: LIQUID
Manufacturer: THE BIGBOND LLC
Category: otc | Type: HUMAN OTC DRUG LABEL
Date: 20200507

ACTIVE INGREDIENTS: ALCOHOL 21 mL/30 mL
INACTIVE INGREDIENTS: FD&C YELLOW NO. 5; WATER; FD&C BLUE NO. 1; AMINOMETHYLPROPANOL; PROPYLENE GLYCOL; ISOPROPYL ALCOHOL; .ALPHA.-TOCOPHEROL ACETATE; CARBOMER HOMOPOLYMER, UNSPECIFIED TYPE; ALOE VERA LEAF; CAPRYLYL GLYCOL; GLYCERIN; ISOPROPYL MYRISTATE

DOSAGE AND ADMINISTRATION

1.5m1-3 5ml/time; Store below 110°F (43°C) ; May discolor certain fabrics of surfaces

keep out of reach of children

INACTIVE INGREDIENT

Water, Isopropyl Alcohol, Aloe Barbadensis Leaf Juice, Caprylyl Glycol, Glycerin, Propylene Glycol ,Isopropyl Myristate, Tocopheryl Acetate, Carbomer, Aminomethyl Propanol, Blue 1(CI 42090), Yellow 5(CI 19140)

INDICATIONS AND USAGE

Take appropriate amount of this product to moisten your hands and rub for one minute until the liquid covers the whole surface

keep out of reach of children

PURPOSE

Disinfection
Sterilization
No Rinseing

ACTIVE INGREDIENT

Ethyl alcohol